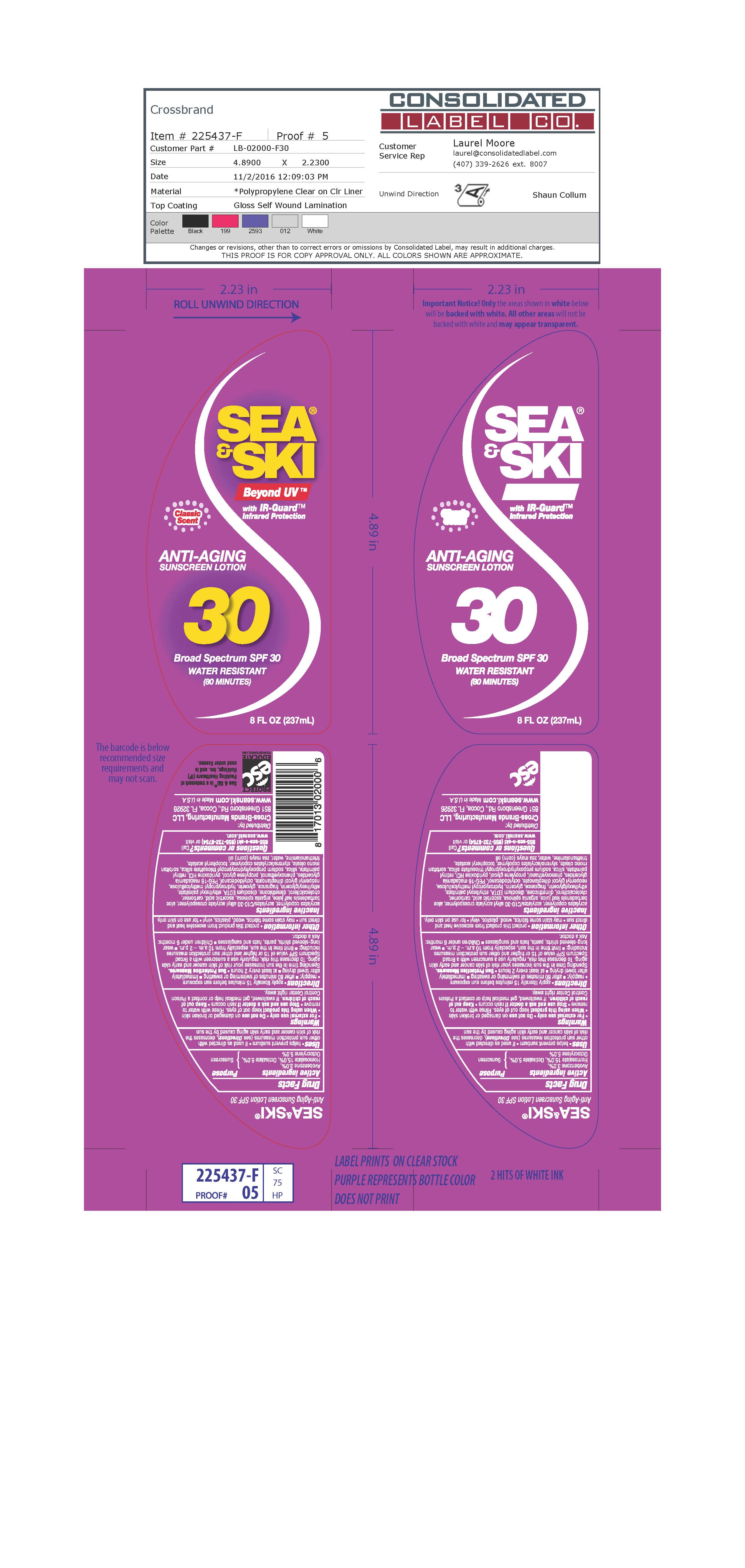 DRUG LABEL: gp sunscreen
NDC: 71153-2000 | Form: LOTION
Manufacturer: Cross-Brands Manufacturing, LLC
Category: otc | Type: HUMAN OTC DRUG LABEL
Date: 20161222

ACTIVE INGREDIENTS: AVOBENZONE 3 g/1 mL; HOMOSALATE 15 g/1 mL; OCTISALATE 5 g/1 mL; OCTOCRYLENE 5 g/1 mL
INACTIVE INGREDIENTS: ALOE VERA LEAF

Sea & Ski GP Sunscreen Lotion